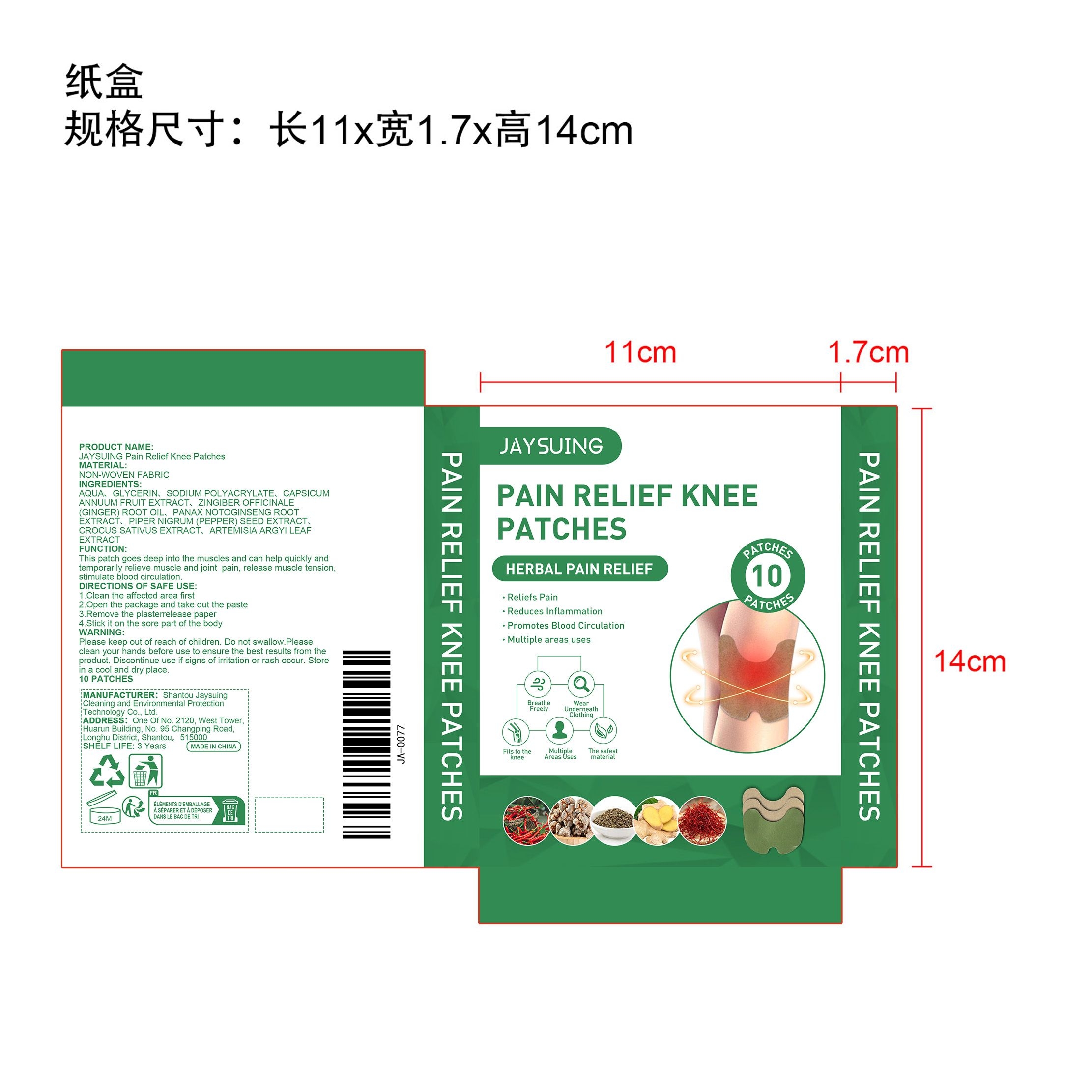 DRUG LABEL: JAYSUING Pain Relief Knee Patches
NDC: 85060-004 | Form: PATCH
Manufacturer: Shantou Jaysuing Cleaning and Environmental Protection Technology Co., Ltd.
Category: otc | Type: HUMAN OTC DRUG LABEL
Date: 20251127

ACTIVE INGREDIENTS: PANAX NOTOGINSENG ROOT 0.002 mg/10 mg; PIPER NIGRUM (PEPPER) SEED OIL 0.002 mg/10 mg; ZINGIBER OFFICINALE (GINGER) ROOT OIL 0.002 mg/10 mg; ARTEMISIA ARGYI LEAF 0.002 mg/10 mg; CROCUS SATIVUS FLOWER 0.002 mg/10 mg
INACTIVE INGREDIENTS: SODIUM POLYACRYLATE STARCH (7 MICROMETER PARTICLE) 0.5 mg/10 mg; CAPSICUM ANNUUM WHOLE 0.002 mg/10 mg; GLYCERIN 2 mg/10 mg; AQUA 7.488 mg/10 mg

ACTIVE INGREDIENT

CAPSICUM ANNUUM FRUIT EXTRACT、
ZINGIBER OFFICINALE (GINGER) ROOT OIL、
PANAX NOTOGINSENG ROOT EXTRACT、
PIPER NIGRUM (PEPPER) SEED EXTRACT、
CROCUS SATIVUS EXTRACT、
ARTEMISIA ARGYI LEAF EXTRACT

PURPOSE

Reliefs Pain
Reduces Inflammation
Promotes Blood Circulation
Multiple areas uses

WARNINGS

Please keep out of reach of children. Do not swallow.Please clean your hands before use to ensure the best results from the product. Discontinue use if signs of irritation or rash occur. Store in a cool and dry place.

WHEN USING

1.Clean the affected area first
2.Open the package and take out the paste
3.Remove the plasterrelease paper
4.Stick it on the sore part of the body

DO NOT USE

Discontinue use if signs of irritation or rash occur.

STOP USE

Discontinue use if signs of irritation or rash occur.

KEEP OUT OF REACH OF CHILDREN

Please keep out of reach of children. Do not swallow.

STORAGE AND HANDLING

Store in a cool and dry place.

INACTIVE INGREDIENT

AQUA、
GLYCERIN、
SODIUM POLYACRYLATE